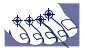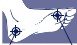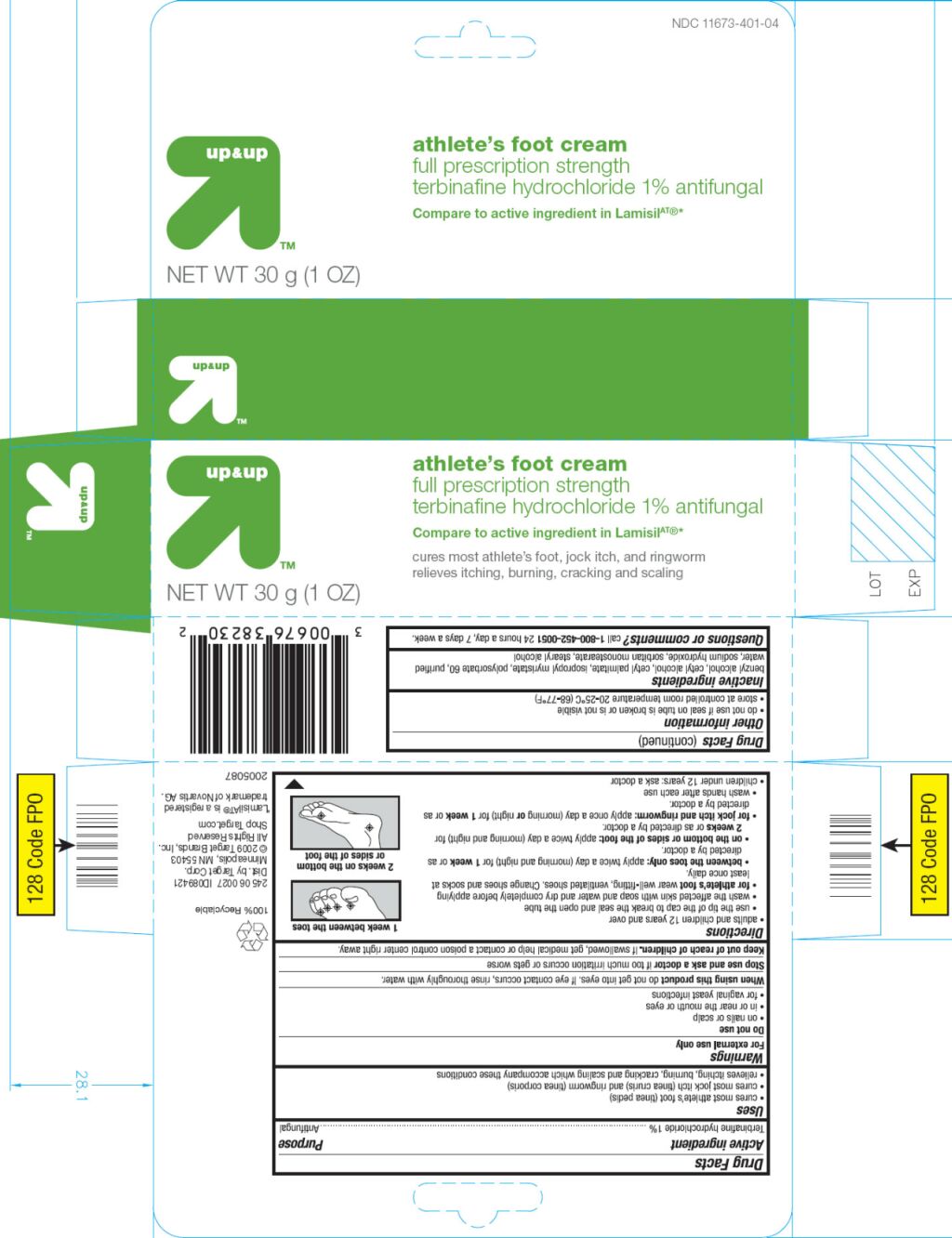 DRUG LABEL: athletes foot
NDC: 11673-401 | Form: CREAM
Manufacturer: Target Corporation
Category: otc | Type: HUMAN OTC DRUG LABEL
Date: 20090819

ACTIVE INGREDIENTS: TERBINAFINE HYDROCHLORIDE 10 mg/1 g
INACTIVE INGREDIENTS: BENZYL ALCOHOL; CETYL ALCOHOL; CETYL PALMITATE; ISOPROPYL MYRISTATE; POLYSORBATE 60; WATER; SODIUM HYDROXIDE; SORBITAN MONOSTEARATE; STEARYL ALCOHOL

Drug Facts

Active ingredient

Terbinafine hydrochloridel 1%

Purpose

Antifungal

Uses

- cures most athlete’s foot (tinea pedis)
- cures most jock itch (tinea cruris) and ringworm (tinea corporis)
- relieves itching, burning, cracking and scaling which accompany these conditions

Warnings

For external use only

Do not use

- on nails or scalp
- in or near the mouth or eyes
- for vaginal yeast infections

When using this product do not get into eyes. If eye contact occurs, rinse thoroughly with water

Stop use and ask a doctor if too much irritation occurs or gets worse

Keep out of reach of children. If swallowed, get medical help or contact a poison control center right away.

Directions

- adults and children 12 years and over
  - use the tip of the cap to break the seal and open the tube
  - wash the affected skin with soap and water and dry completely before applying
  - for athlete’s foot wear well-fitting, ventilated shoes. Change shoes and socks at least once daily.
    - between the toes only: apply twice a day (morning and night) for 1 week or as

directed by a doctor

1 week between the toes

-
  -
    - on the bottom or sides of the foot: apply twice a day (morning and night) for 2 weeks or as directed by a doctor
- 2 weeks on the bottom or sides of the foot
  - for jock itch and ringworm: apply once a day (morning or night) for 1 week or as directed by a doctor
  - wash hands after each use
- children under 12 years: ask a doctor

Other information

Store at controlled room temperature 20-25°C (68-77°F)

See crimp for lot number and expiration date

Do not use if seal on tube is broken or is not visible

Questions? call 1-800-452-0051 24 hours a day, 7 days a week

100% Quality Guaranteed 888.309.9030

Inactive ingredients

benzyl alcohol, cetyl alcohol, cetyl palmitate, isopropyl myristate, polysorbate 60, purified water, sodium hydroxide, sorbitan monostearate, stearyl alcohol

Distributed by

Target Corporation

1000 Nicolet Mall

Minneapolis, MN 55403

©2008

Primary Display Pane

athlete's foot cream